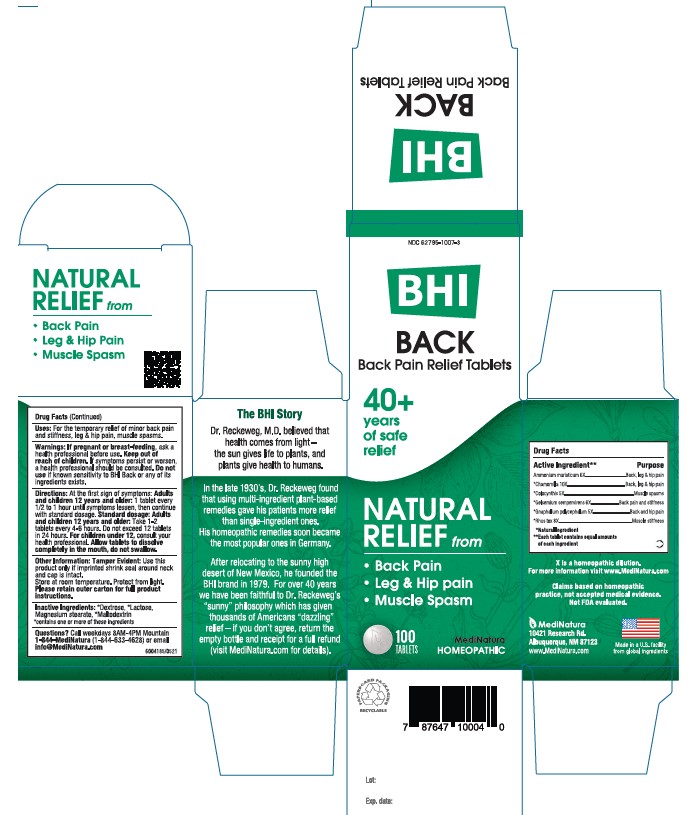 DRUG LABEL: BHI Back
NDC: 62795-1007 | Form: TABLET
Manufacturer: MediNatura Inc
Category: homeopathic | Type: HUMAN OTC DRUG LABEL
Date: 20230523

ACTIVE INGREDIENTS: AMMONIUM CHLORIDE 6 [hp_X]/1 1; MATRICARIA RECUTITA 10 [hp_X]/1 1; CITRULLUS COLOCYNTHIS FRUIT PULP 5 [hp_X]/1 1; GELSEMIUM SEMPERVIRENS ROOT 6 [hp_X]/1 1; PSEUDOGNAPHALIUM OBTUSIFOLIUM 5 [hp_X]/1 1; TOXICODENDRON PUBESCENS LEAF 8 [hp_X]/1 1
INACTIVE INGREDIENTS: LACTOSE; MAGNESIUM STEARATE; DEXTROSE; MALTODEXTRIN

BHI Back

ACTIVE INGREDIENT

Each tablet contains: Ammonium muriaticum 6X, *Chamomilla 10X, *Colocynthis 5X, *Gelsemium sempervirens 6X, *Gnaphalium polycephalum 5X, *Rhus toxicodendron 8X 50 mg each.

*Natural Ingredients

INACTIVE INGREDIENT

Inactive Ingredients: **Dextrose, ** Lactose, Magnesium Stearate, **Maltodextrin
**contains one or more of these ingredients.

PURPOSE

Back Pain Relief Tablets

Relieves:

• Back Pain

• Leg & Hip Pain

• Muscle Spasm

USES

For the temporary relief of minor back pain, leg & hip pain, muscle spasm

DIRECTIONS

At first sign of symptoms:

Adults and children 12 years and older: 1 tablet every 1/2 to 1 hour until symptoms lessen, then continue with standard dosage.

Standard dosage: Adults and children 12 years and older: take 1-2 tablets 4 to 6 hours. Do not exceed 12 tablets in 24 hours. For children under 12, consult your health professional.

Allow tablets to dissolve completely in the mouth, do not swallow.

WARNINGS

Warnings: If pregnant or breast-feeding, ask a health professional before use. Keep out of reach of children. If symptoms persist or worsen, a health professional should be consulted. Do not use if known sensitivity to BHI Back or any of its ingredients exists.

KEEP OUT OF REACH OF CHILDREN